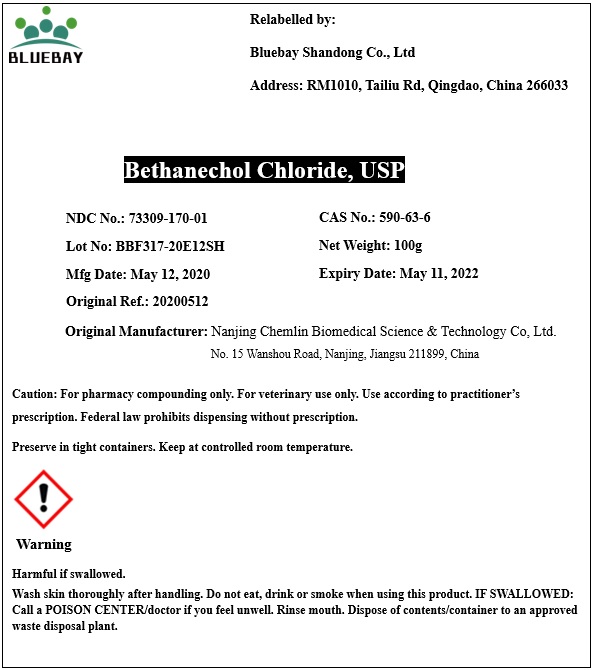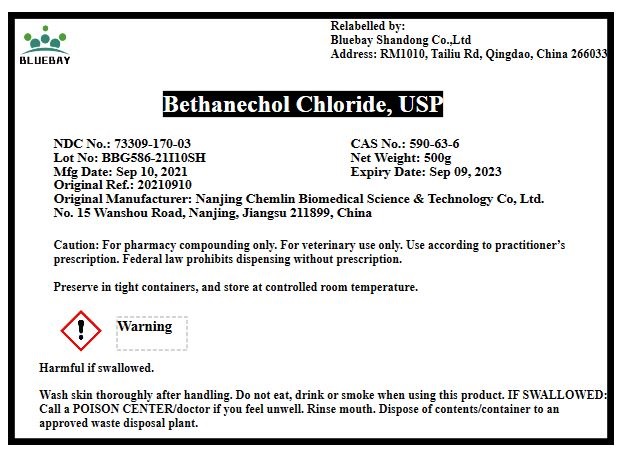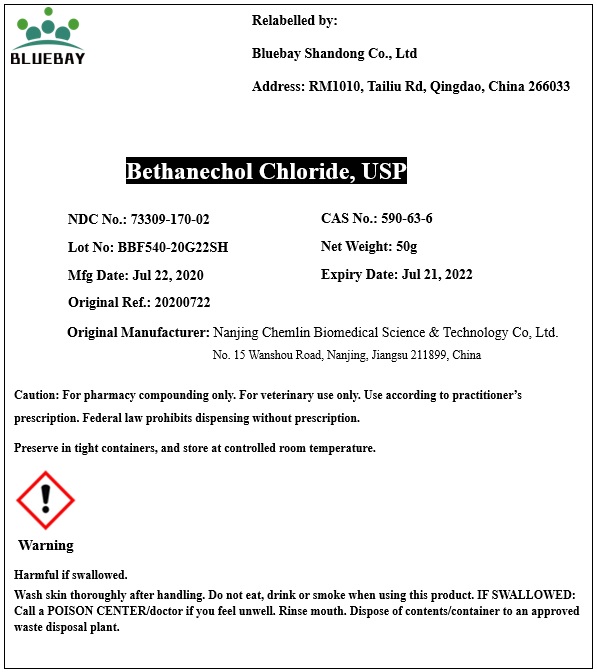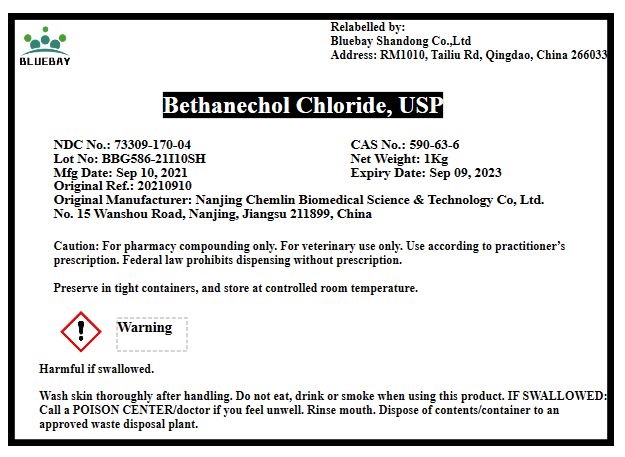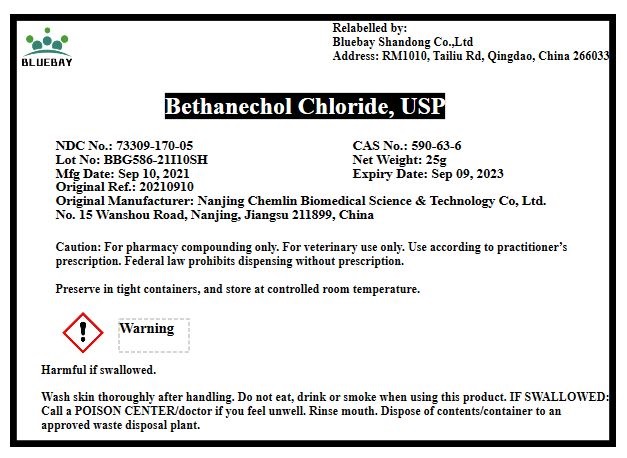 DRUG LABEL: Bethanechol Chloride
NDC: 73309-170 | Form: POWDER
Manufacturer: BLUEBAY SHANDONG CO.,LTD
Category: other | Type: BULK INGREDIENT
Date: 20211119

ACTIVE INGREDIENTS: BETHANECHOL CHLORIDE 1 g/1 g

Bethanechol Chloride